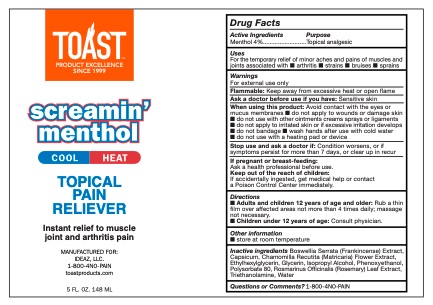 DRUG LABEL: Toast Screamin Menthol
NDC: 78983-103 | Form: CREAM
Manufacturer: IDEAZ, LLC
Category: otc | Type: HUMAN OTC DRUG LABEL
Date: 20250616

ACTIVE INGREDIENTS: MENTHOL 4 g/100 g
INACTIVE INGREDIENTS: ROSMARINUS OFFICINALIS (ROSEMARY) LEAF OIL; GLYCERIN; TRIETHANOLAMINE; PHENOXYETHANOL; WATER; CAPSICUM; ETHYLHEXYLGLYCERIN; ISOPROPYL ALCOHOL; POLYSORBATE 80; MATRICARIA CHAMOMILLA FLOWERING TOP OIL; BOSWELLIA SERRATA OIL

Toast Screamin' Menthol - 78983-103

Active Ingredient

Menthol 4%

Purpose

Topical analgesic

Uses

for the temporary relief of minor aches and pains of

muscles and joints associated with ■ arthritis ■ strains

■ bruises ■ sprains

Warnings

For external use only

Flammable: Keep away from excessive heat or open flame

Ask a doctor before use if you have: Sensitive skin

When using this product

Avoid contact with the eyes or

mucus membranes ■ do not apply to wounds or damage skin

■ do not use with other ointments creams sprays or ligaments

■ do not apply to irritated skin or if excessive irritation develops

■ do not bandage ■ wash hands after use with cold water

■ do not use with a heating pad or device

Stop using consult a doctor if

Condition worsens, or if

symptoms persist for more than 7 days, or clear up in recur

Keep out of reach of children

If swallowed, get medical help

or contact a Poison Control Center immediately.

If pregnant or breast-feeding

ask a healthcare professional before use.

Directions

■ Adults and children 12 years of age and older: Rub a thin

film over affected areas not more than 4 times daily; massage

not necessary.

■ Children under 12 years of age: Consult physician.

Other information

■ store at room temperature

Inactive ingredients

Boswellia Serrata (Frankincense) Extract, Capsicum, Chamomilla Recutita (Matricaria) Flower Extract, Ethylhexylglycerin, Glycerin, Isopropyl Alcohol, Phenoxyethanol, Polysorbate 80, Rosmarinus Officinalis (Rosemary) Leaf Extract, Triethanolamine, Water

Questions or Comments?

1-800-4NO-PAIN